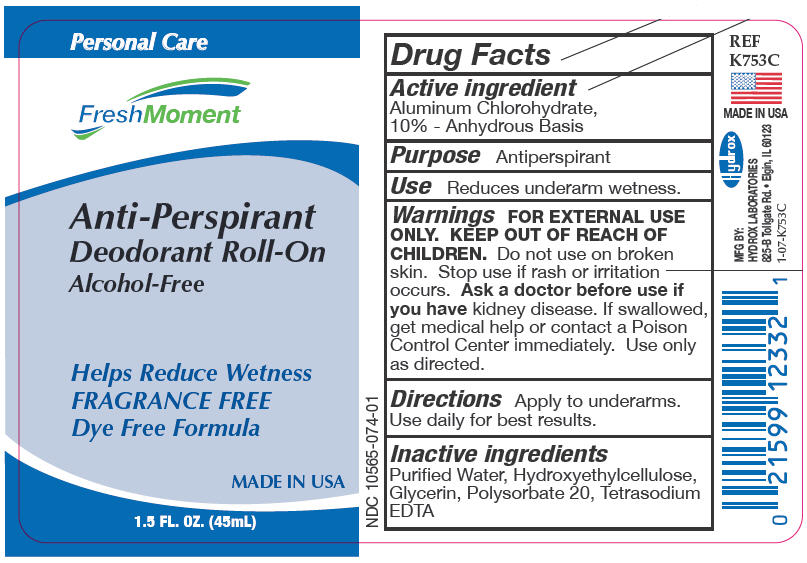 DRUG LABEL: Anti-Perspirant Deodorant Roll-On
NDC: 10565-074 | Form: LIQUID
Manufacturer: Hydrox Laboratories
Category: otc | Type: HUMAN OTC DRUG LABEL
Date: 20260112

ACTIVE INGREDIENTS: ALUMINUM CHLOROHYDRATE 10 g/100 mL
INACTIVE INGREDIENTS: WATER; HYDROXYETHYL CELLULOSE, UNSPECIFIED; GLYCERIN; POLYSORBATE 20; EDETATE SODIUM

Anti-Perspirant Deodorant Roll-On Unscented

Drug Facts

Active ingredient

Aluminum Chlorohydrate, 10% - Anhydrous Basis

Purpose

Antiperspirant

Use

Reduces underarm wetness.

Warnings

FOR EXTERNAL USE ONLY.

KEEP OUT OF REACH OF CHILDREN.

Do not use on broken skin.

Stop use if rash or irritation occurs.

Ask a doctor before use if you havekidney disease. If swallowed, get medical help or contact a Poison Control Center immediately. Use only as directed.

Directions

Apply to underarms. Use daily for best results.

Inactive ingredients

Purified Water, Hydroxyethylcellulose, Glycerin, Polysorbate 20, Tetrasodium EDTA

PRINCIPAL DISPLAY PANEL

Personal Care

FreshMoment

Anti-Perspirant

Deocorant Roll-On

Alcohol Free

Helps Reduce Wetness

Fragrance Free

Dye Free Formula

Made in USA